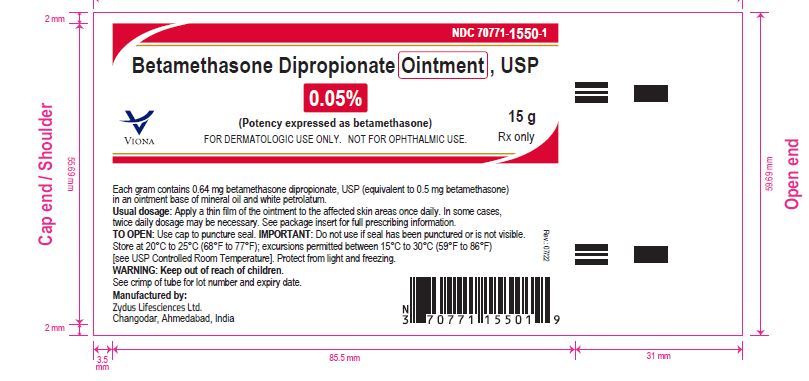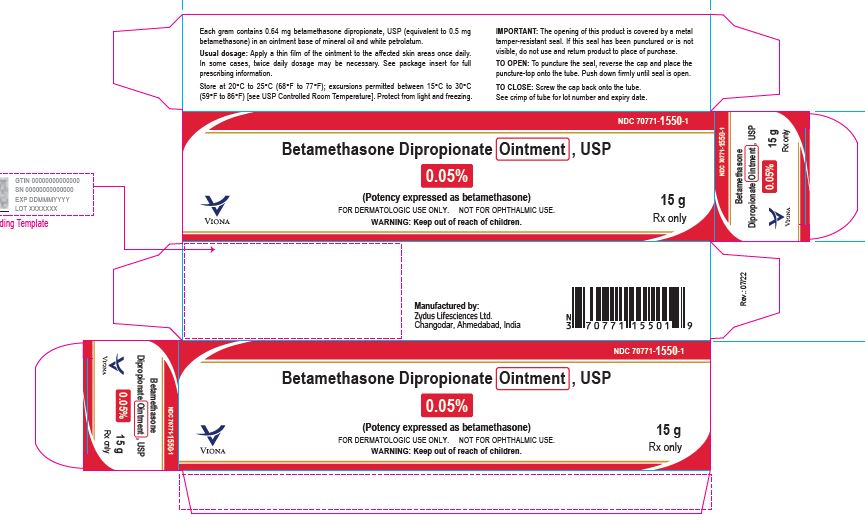 DRUG LABEL: betamethasone dipropionate
NDC: 70771-1550 | Form: OINTMENT
Manufacturer: Zydus Lifesciences Limited
Category: prescription | Type: HUMAN PRESCRIPTION DRUG LABEL
Date: 20221105

ACTIVE INGREDIENTS: BETAMETHASONE DIPROPIONATE 0.5 mg/1 g
INACTIVE INGREDIENTS: MINERAL OIL; PETROLATUM

BETAMETHASONE DIPROPIONATE
OINTMENT USP, 0.05%

PACKAGE LABEL.PRINCIPAL DISPLAY PANEL

Betamethasone Dipropionate Ointment USP, 0.05%

NDC 70771-1550-1 in tube of 15 gm

Rx Only